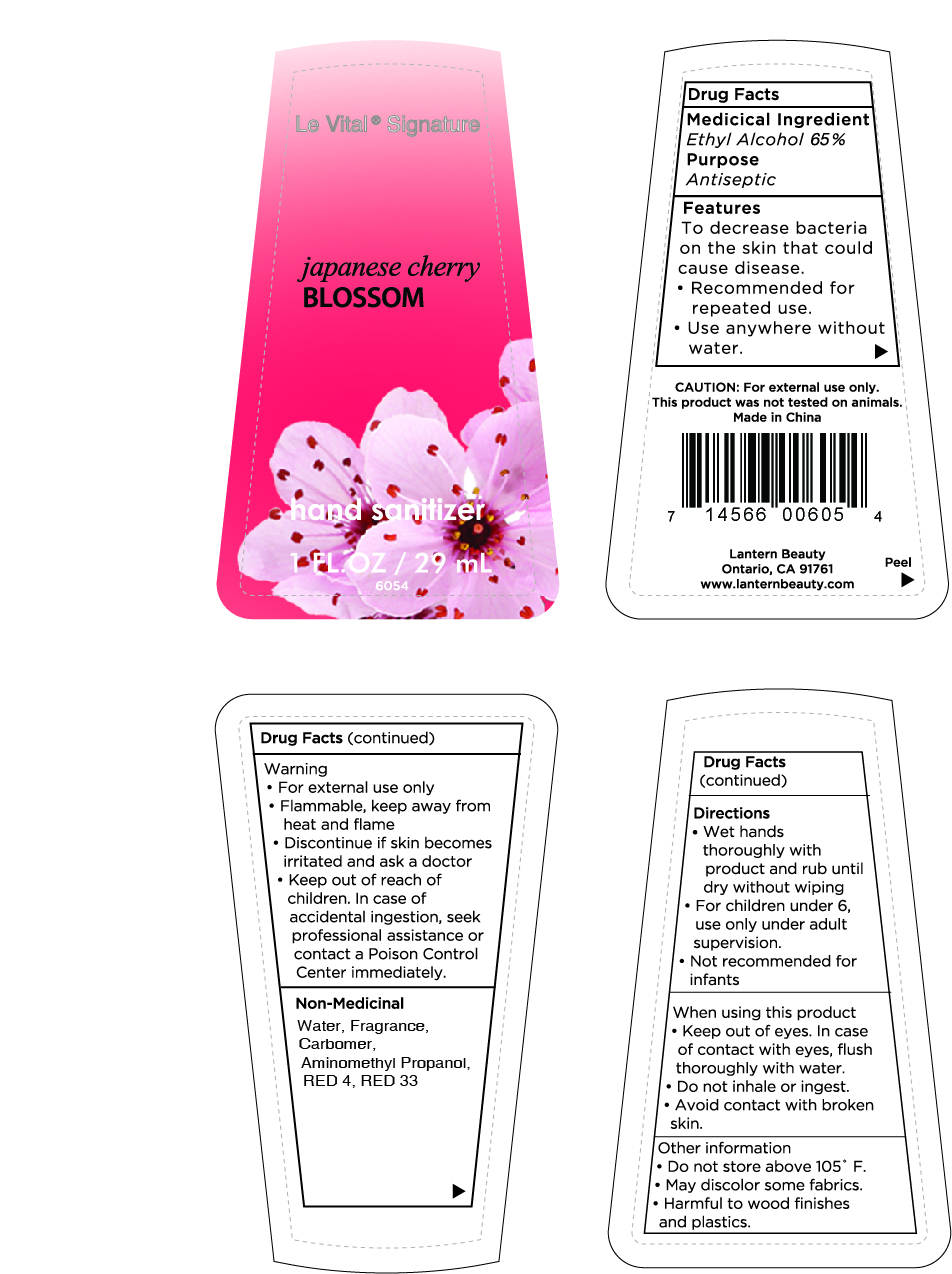 DRUG LABEL: Hand sanitizer 29ml
NDC: 54860-415 | Form: LIQUID
Manufacturer: Shenzhen Lantern Scicence Co.,Ltd.
Category: otc | Type: HUMAN OTC DRUG LABEL
Date: 20250205

ACTIVE INGREDIENTS: ALCOHOL 65 mL/100 mL
INACTIVE INGREDIENTS: FRAGRANCE 13576 0.3 mL/100 mL; WATER 34.3397 mL/100 mL; CARBOMER 940 0.26 mL/100 mL; FD&C RED NO. 4 0.0002 mL/100 mL; 1-AMINOCYCLOPROPANOL 0.1 mL/100 mL; D&C RED NO. 33 0.0001 mL/100 mL

Hand sanitizer 29ml

Drug Facts

Active Ingredient

Active Ingredient Purpose

Ethyl Alcohol 65%（V/V） Antiseptic

Use

Hand sanitizer helps to reduce bacteria that potentially can cause disease.For use when soap and water are not available.

Use(s)

To decrease bacteria on the skin that could cause disease.Recommended for repeated use.

Warning

For external use only-hands

Flammable.Keep away from heat and flame.

WARNINGS AND PRECAUTIONS

For external use only.

Flammable, keep away from heat and flame.

STOP USE

Discontinue if skin becomes irritated and ask a doctor .

Keep out of reach of children. In case of accidental ingestion, seek professional assistance or contact a poson control center immediately.

keep out of reach of children

If accidentally ingested, please seek professional assistance immediately or contact the Poison Control Center.

DOSAGE AND ADMINISTRATION

Recommended for repeated use.

use anywhere without water.

Inactive ingredients

Water, Fragrance,Carbomer,Aminomethyl Propanol,RED 4,RED 33.

Directions

Wet hands thoroughly with product and rub until dry without wiping.Children under 6,use only with adult supervision.

When using this product

keep out of eyes. In case of contact with eyes, flush thoroughly with water.

Do not inhale or ingest.

Avoid contact with broken skin.

Other information

Do not store above 105F.

May discolor some fabrics.

Harmful to wood finishes and plastics.

When using this product

Do not use in or near eyes,In case of eye contact ,flush eyes thoroughly with water. Discontinue if skin becomes irritated and ask for a doctor.

Other information

store below 105℉

May discolor some fabrics and surfaces.

Purpose

Antiseptic

Packaging